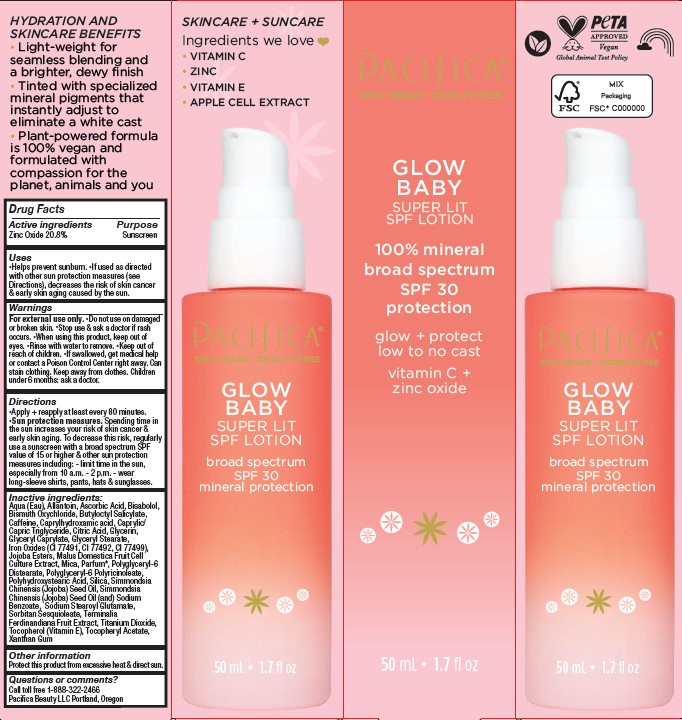 DRUG LABEL: Glow Baby Super Lit SPF 30
NDC: 61197-217 | Form: SPRAY
Manufacturer: Pacifica Beauty, LLC
Category: otc | Type: HUMAN OTC DRUG LABEL
Date: 20250103

ACTIVE INGREDIENTS: ZINC OXIDE 20.8 g/100 mL
INACTIVE INGREDIENTS: MALUS DOMESTICA WHOLE; POLYGLYCERYL-6 POLYRICINOLEATE; SILICON DIOXIDE; POLYHYDROXYSTEARIC ACID (2300 MW); MICA; CAFFEINE; CAPRYLHYDROXAMIC ACID; SODIUM STEAROYL GLUTAMATE; KAKADU PLUM; XANTHAN GUM; FERRIC OXIDE RED; FERROSOFERRIC OXIDE; TOCOPHEROL; ALPHA-TOCOPHEROL ACETATE; JOJOBA OIL; SODIUM BENZOATE; SORBITAN SESQUIOLEATE; TITANIUM DIOXIDE; .ALPHA.-BISABOLOL, (+)-; FERRIC OXIDE YELLOW; ASCORBIC ACID; HYDROLYZED JOJOBA ESTERS (ACID FORM); ALLANTOIN; GLYCERYL CAPRYLATE; BISMUTH OXYCHLORIDE; BUTYLOCTYL SALICYLATE; MEDIUM-CHAIN TRIGLYCERIDES; WATER; CITRIC ACID MONOHYDRATE; GLYCERIN; GLYCERYL STEARATE SE

Glow Baby Super Lit SPF 30 Lotion

Active ingredients Purpose

Zinc Oxide 20.8% Sunscreen

Uses

Helps prevent sunburn. If used as directed with other sun protection measures (see Directions), decreases the risk of skin cancer & early skin aging caused by the sun.

INDICATIONS AND USAGE

If used as directed with other sun protection measures (see Directions), decreases the risk of skin cancer & early skin aging caused by the sun.

Warnings

For external use only. Do not use on damaged or broken skin. Stop use & ask a doctor if rash occurs. When using this product, keep out of eyes. Rinse with water to remove. Keep out of reach of children. If swallowed, get medical help or contact a Poison Control Center right away. Can stain clothing. Keep away from clothes. Children under 6 months: ask a doctor.

Keep out of reach of children.

Directions

Apply and reapply at least every 80 minutes. Sun protection measures. Spending time in the sun increases your risk of skin cancer & early skin aging. To decrease this risk, regularly use a sunscreen with a broad spectrum SPF value of 15 or higher & other sun protection measures including: - limit time in the sun, especially from 10 a.m. - 2 p.m. - wear long-sleeve shirts, pants, hats & sunglasses.

Inactive ingredients:

Aqua (Eau), Allantoin, Ascorbic Acid, Bisabolol, Bismuth Oxychloride, Butyloctyl Salicylate, Caffeine, Caprylhydroxamic acid, Caprylic/ Capric Triglyceride, Citric Acid, Glycerin, Glyceryl Caprylate, Glyceryl Stearate, Iron Oxides (CI 77491, CI 77492, CI 77499), Jojoba Esters, Malus Domestica Fruit Cell Culture Extract, Mica, Parfum*, Polyglyceryl-6 Distearate, Polyglyceryl-6 Polyricinoleate, Polyhydroxystearic Acid, Silica, Simmondsia Chinensis (Jojoba) Seed Oil, Simmondsia Chinensis (Jojoba) Seed Oil (and) Sodium Benzoate, Sodium Stearoyl Glutamate, Sorbitan Sesquioleate, Terminalia Ferdinandiana Fruit Extract, Titanium Dioxide, Tocopherol (Vitamin E), Tocopheryl Acetate, Xanthan Gum.

Other information

Protect this product from excessive heat & direct sun.

Questions or comments?

Call toll free 1-888-322-2466
Pacifica Beauty LLC Portland, Oregon